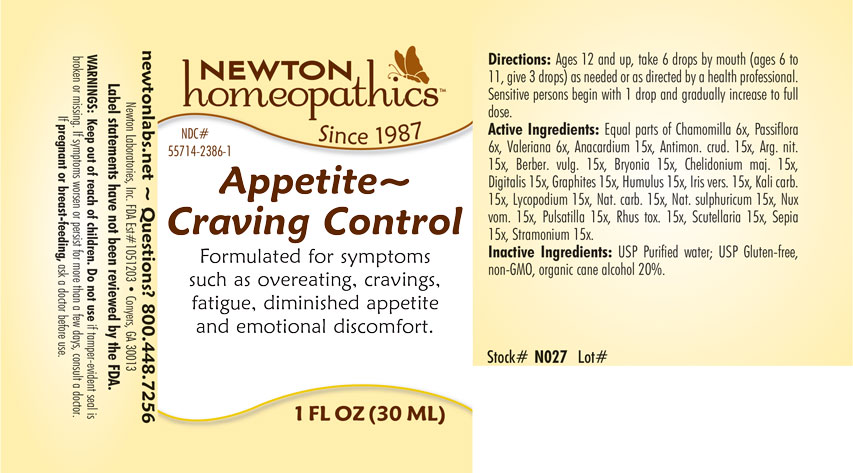 DRUG LABEL: Appetite - Craving Control
NDC: 55714-2386 | Form: LIQUID
Manufacturer: Newton Laboratories, Inc.
Category: homeopathic | Type: HUMAN OTC DRUG LABEL
Date: 20250206

ACTIVE INGREDIENTS: LYCOPODIUM CLAVATUM SPORE 15 [hp_X]/1 mL; SEMECARPUS ANACARDIUM JUICE 15 [hp_X]/1 mL; ANTIMONY TRISULFIDE 15 [hp_X]/1 mL; SILVER NITRATE 15 [hp_X]/1 mL; BERBERIS VULGARIS ROOT BARK 15 [hp_X]/1 mL; BRYONIA ALBA ROOT 15 [hp_X]/1 mL; CHELIDONIUM MAJUS 15 [hp_X]/1 mL; DIGITALIS 15 [hp_X]/1 mL; GRAPHITE 15 [hp_X]/1 mL; HOPS 15 [hp_X]/1 mL; IRIS VERSICOLOR ROOT 15 [hp_X]/1 mL; POTASSIUM CARBONATE 15 [hp_X]/1 mL; SODIUM CARBONATE 15 [hp_X]/1 mL; SODIUM SULFATE 15 [hp_X]/1 mL; STRYCHNOS NUX-VOMICA SEED 15 [hp_X]/1 mL; PULSATILLA VULGARIS 15 [hp_X]/1 mL; TOXICODENDRON PUBESCENS LEAF 15 [hp_X]/1 mL; SCUTELLARIA LATERIFLORA 15 [hp_X]/1 mL; SEPIA OFFICINALIS JUICE 15 [hp_X]/1 mL; DATURA STRAMONIUM 15 [hp_X]/1 mL; MATRICARIA RECUTITA 6 [hp_X]/1 mL; PASSIFLORA INCARNATA FLOWERING TOP 6 [hp_X]/1 mL; VALERIAN 6 [hp_X]/1 mL
INACTIVE INGREDIENTS: WATER; ALCOHOL

Appetite 2386L

INDICATIONS & USAGE SECTION

Formulated for symptoms such as overeating, cravings, fatigue, diminished appetite and emotional discomfort..

WARNINGS SECTION

WARNINGS: Keep out of reach of children. Do not use if tamper-evident seal is broken or missing. If symptoms worsen or persist for more than a few days, consult a doctor. If pregnant or breast-feeding, ask a doctor before use.

OTC - KEEP OUT OF REACH OF CHILDREN SECTION

Keep out of reach of children.

OTC - PREGNANCY OR BREAST FEEDING SECTION

If pregnant or breast-feeding, ask a doctor before use.

QUESTIONS SECTION

newtonlabs.net – Questions? 800.448.7256

Newton Laboratories, Inc. FDA Est # 1051203 - Conyers, GA 30013

INACTIVE INGREDIENT SECTION

Inactive Ingredients: USP Purified Water; USP Gluten-free, non-GMO, organic cane alcohol 20%.

OTC - PURPOSE SECTION

Formulated for associated symptoms such as overeating, cravings, fatigue, diminished appetite and emotional discomfort.

OTC - ACTIVE INGREDIENT SECTION

Equal parts of Chamomilla 6x, Passiflora 6x, Valeriana 6x, Anacardium orientale 15x, Antimon.crud. 15x, Arg. nit. 15x, Berber. vulg. 15x, Bryonia 15x,Chelidonium maj.15x, Digitalis 15x, Graphites 15x, Humulus 15x,Iris vers. 15x, Kali carb. 15x, Lycopodium 15x, Nat. carb. 15x ,Nat. sulphuricum 15x, Nux vom. 15x, Pulsatilla 15x, Rhus tox.15x, Scutellaria lateriflora 15x, Sepia 15x, Stramonium 15x.

DOSAGE & ADMINISTRATION SECTION

Directions: Ages 12 and up, take 6 drops by mouth (ages 6 to 11, give 3 drops) as needed or as directed by a health professional. Sensitive persons begin with 1 drop and gradually increase to full dose.